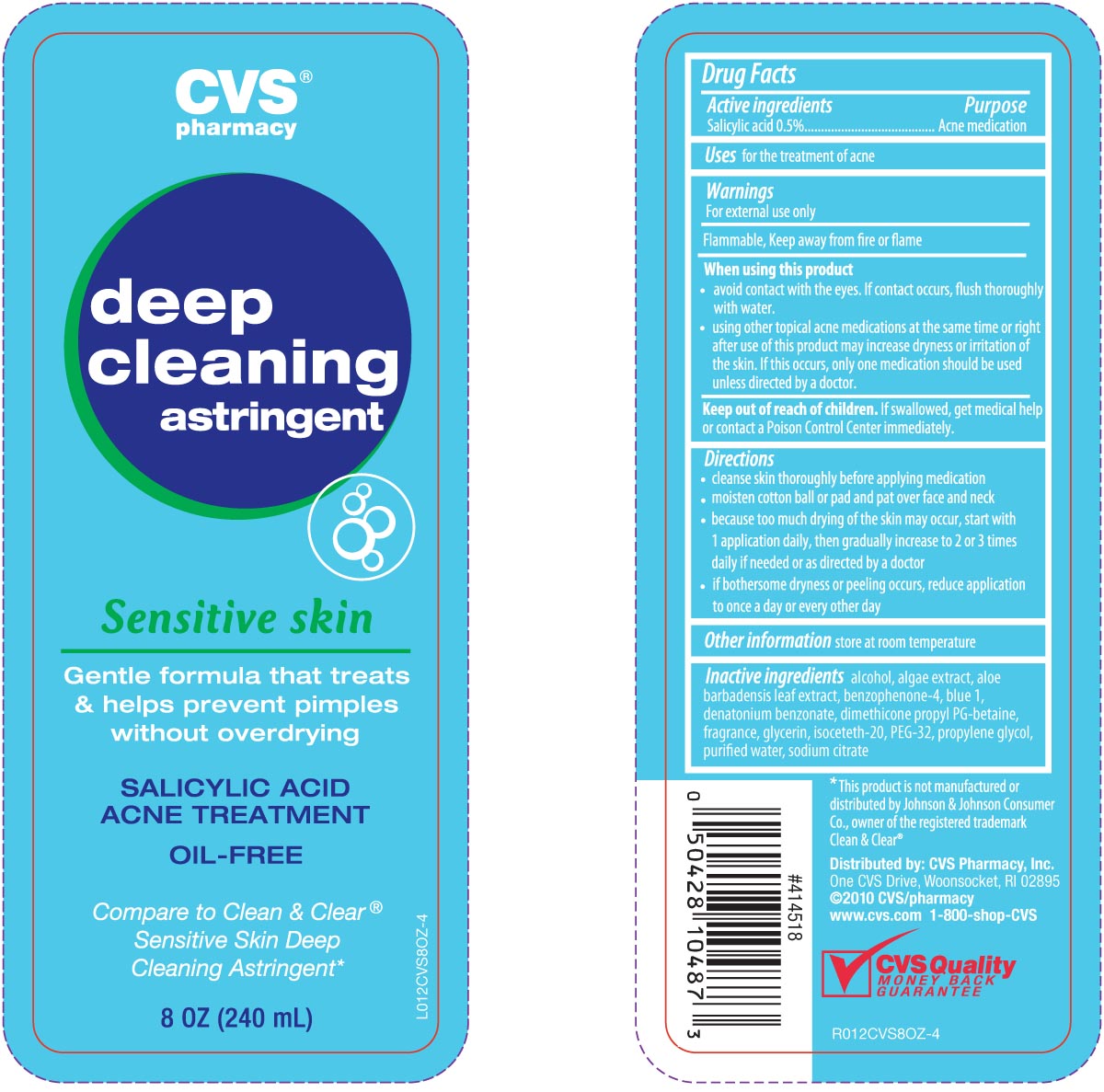 DRUG LABEL: CVS Deep Cleansing Astringent
NDC: 59779-811 | Form: LIQUID
Manufacturer: CVS Pharmacy
Category: otc | Type: HUMAN OTC DRUG LABEL
Date: 20100708

ACTIVE INGREDIENTS: SALICYLIC ACID 5 mg/1 mL
INACTIVE INGREDIENTS: WATER; ALCOHOL; ALOE VERA LEAF; BENZOPHENONE; DENATONIUM BENZOATE; LAURAMIDOPROPYL BETAINE; GLYCERIN; ISOCETYL ALCOHOL; PEG-32 STEARATE; PROPYLENE GLYCOL; SODIUM CITRATE; FD&C BLUE NO. 1

DRUG FACTS

Active ingredient Purpose
Salicylic Acid 0.5%.........................................Acne medication

PURPOSE

Uses for the treatment of acne

Keep out of reach of children. If swallowed, get medical help or contact a
Poison Control Center immediately.

INDICATIONS AND USAGE

Uses for the treatment of acne

Warnings
For external use only
Flammable, Keep away from fire or flame
When using this product
- avoid contact with eyes. If contact occurs, flush thoroughly with water.
- using other topical acne medications at the same time or right after use of this product,
may increase dryness or irritation of the skin. If this occurs, only one medication should
be used unless directed by a doctor.
Keep out of reach of children. If swallowed, get medical help or contact a
Poison Control Center right away.

Directions
- cleanse skin thoroughly before applying medication
- moisten cotton ball or pad and pat over face and neck
- because too much drying of the skin may occur, start with 1 application daily,
then gradually increase to 2 to 3 times daily if needed or as directed by a doctor
- if bothersome dryness or peeling occurs, reduce application to once a day or every other day
Other information store at room temperature

Inactive Ingredients
alcohol, alge extract, aloe barbadensis leaf extract, benzophenone-4, blue-1,
dentatonium benzonate, dimethicone propyl PG-betaine, fragrance, glycerin,
isoceteth-20, PEG-32, propylene glycol, purified water, sodium citrate